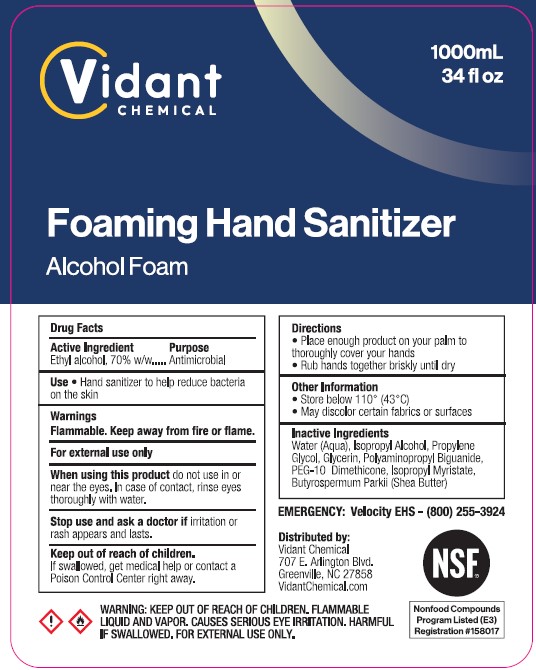 DRUG LABEL: FOAMING HAND

NDC: 83019-102 | Form: SOAP
Manufacturer: Draco Hygienic Products Inc.
Category: otc | Type: HUMAN OTC DRUG LABEL
Date: 20241008

ACTIVE INGREDIENTS: ALCOHOL 70 mL/100 mL
INACTIVE INGREDIENTS: POLYAMINOPROPYL BIGUANIDE; ISOPROPYL MYRISTATE; SHEA BUTTER; WATER; ISOPROPYL ALCOHOL; PROPYLENE GLYCOL; GLYCERIN; PEG-10 DIMETHICONE (200 CST)

DRACO (as PLD) - VIDANT CHEMICAL - FOAMING HAND SOAP (83019-102)

ACTIVE INGREDIENT

ETHYL ALCOHOL 70% W/W

PURPOSE

ANTIMICROBIAL

USE

HAND SANITIZER TO HELP REDUCE BACTERIA ON THE SKIN.

WARNINGS

FLAMMABLE. KEEP AWAY FROM FIRE OR FLAME.

For external use only.

When using this product do not use in or near the eyes. In case of contact, rinse eyes thoroughly with water.

Stop use this product and ask a doctor if irritation or rash appears and lasts.

Keep out of reach of children
lf swallowed,get medical help or contact Poison Control Center right away.

DIRECTIONS

- Place enough product on your palm to thoroughly cover your hands.
- Rub hands together briskly until dry.

OTHER INFORMATION

- Store below 110° (43°C)
- May discolor certain fabrics or surfaces

INACTIVE INGREDIENTS

Water (Aqua), Isopropyl Alcohol, Propylene Glycol, Glycerin, Polyaminopropyl Biguanide, PEG-10 Dimethicone, Isopropyl Myristate, Butyrospermum Parkii (Shea Butter)